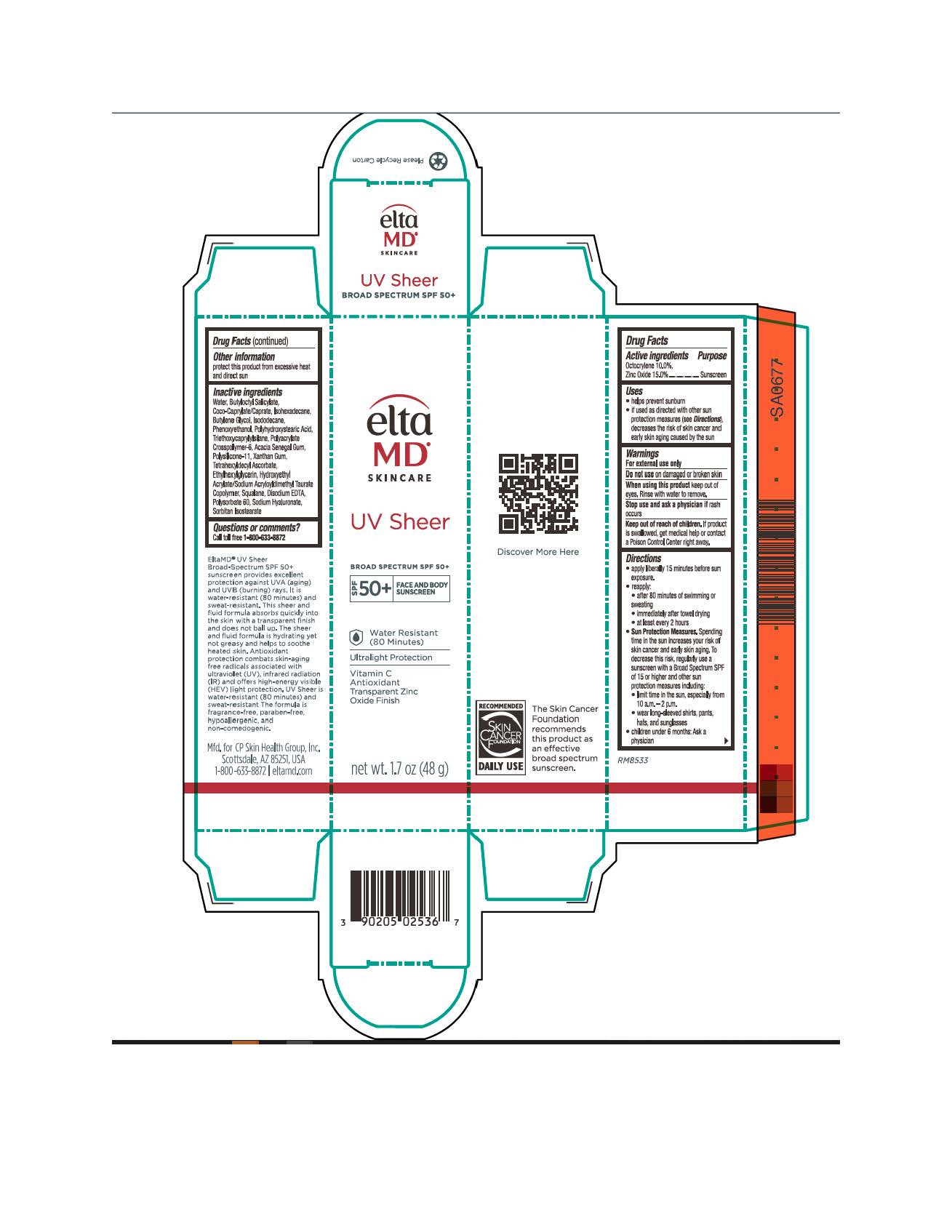 DRUG LABEL: EltaMD UV Sheer
NDC: 72043-2563 | Form: CREAM
Manufacturer: CP Skin Health Group, Inc.
Category: otc | Type: HUMAN OTC DRUG LABEL
Date: 20231205

ACTIVE INGREDIENTS: ZINC OXIDE 150 g/1000 g; OCTOCRYLENE 100 g/1000 g
INACTIVE INGREDIENTS: WATER; HYALURONIC ACID; BUTYLENE GLYCOL; PHENOXYETHANOL; ETHYLHEXYLGLYCERIN; SODIUM HYDROXIDE; BUTYLOCTYL SALICYLATE; ISODODECANE; POLYHYDROXYSTEARIC ACID (2300 MW); TRIETHOXYCAPRYLYLSILANE; ACACIA SENEGAL FLOWER; XANTHAN GUM; TETRAHEXYLDECYL ASCORBATE; EDETATE DISODIUM; DIMETHICONE/VINYL DIMETHICONE CROSSPOLYMER (SOFT PARTICLE); HYDROXYETHYL ACRYLATE/SODIUM ACRYLOYLDIMETHYL TAURATE COPOLYMER (100000 MPA.S AT 1.5%); SQUALANE; POLYSORBATE 60; ISOHEXADECANE; AMMONIUM ACRYLOYLDIMETHYLTAURATE, DIMETHYLACRYLAMIDE, LAURYL METHACRYLATE AND LAURETH-4 METHACRYLATE COPOLYMER, TRIMETHYLOLPROPANE TRIACRYLATE CROSSLINKED (45000 MPA.S)

EltaMD UV Sheer

Warnings

For external use only. Do not use on damaged or broken skin. When using this product keep out of eyes. Rinse with water to remove. Stop use and ask a physician if rash occurs. If product is swallowed get medical help or contact a Poison Control Center right away.

Active Ingredients

Octocrylene 10% Sunscreen
Zinc Oxide 15% Sunscreen

Uses

Helps prevent sunburn. If used as directed with other sun protection measure (See Directions), decreases the risk of skin cancer and early skin aging caused by the sun.

Uses

Helps prevent sunburn. If used as directed with other sun protection measure (See Directions), decreases the risk of skin cancer and early skin aging caused by the sun.

Keep out of reach of children

Directions

Apply liberally 15 minutes before sun exposure. Reapply after 80 minutes of swimming or sweating, immediately after towel drying, at least every 2 hours. Sun Protection Measures: Spending time in the sun increases your risk of skin cancer and early skin aging. To decrease this risk, regularly use a sunscreen with a broad-spectrum SPF of 15 or higher and other sun protection measures including: limit time in the sun, especially from 10 am to 2 pm. Wear long-sleeve shirts, pants, hats, and sunglasses. Children under 6 months: ask a physician

Other Information

Protect this product from excessive heat and direct sun.

Inactive ingredients

water, butyloctyl salicylate, coco-caprylate/caprate, isohexadecane, butylene glycol, isododecane, phenoxyethanol, polyhydroxystearic acid, triethoxycaprylylsilane, polyacrylate crosspolymer-6, acacia Senegal gum, polysilicone-11, xanthan gum, tetrahexyldecyl ascorbate, ethylhexylglycerin, hydroxyethyl acrylate/sodium acryloyldimethyl taurate copolymer, squalene, disodium EDTA, polysorbate 60, sodium hyaluronate, sodium hydroxide

Questions?

Call toll free 1-800-633-8872